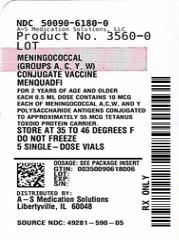 DRUG LABEL: MENQUADFI
NDC: 50090-6180 | Form: INJECTION, SOLUTION
Manufacturer: A-S Medication Solutions
Category: other | Type: VACCINE LABEL
Date: 20230414

ACTIVE INGREDIENTS: NEISSERIA MENINGITIDIS GROUP A CAPSULAR POLYSACCHARIDE TETANUS TOXOID CONJUGATE ANTIGEN 10 ug/0.5 mL; NEISSERIA MENINGITIDIS GROUP C CAPSULAR POLYSACCHARIDE TETANUS TOXOID CONJUGATE ANTIGEN 10 ug/0.5 mL; NEISSERIA MENINGITIDIS GROUP Y CAPSULAR POLYSACCHARIDE TETANUS TOXOID CONJUGATE ANTIGEN 10 ug/0.5 mL; NEISSERIA MENINGITIDIS GROUP W-135 CAPSULAR POLYSACCHARIDE TETANUS TOXOID CONJUGATE ANTIGEN 10 ug/0.5 mL
INACTIVE INGREDIENTS: SODIUM CHLORIDE 3.35 mg/0.5 mL; SODIUM ACETATE ANHYDROUS 1.23 mg/0.5 mL; WATER

HIGHLIGHTS OF PRESCRIBING INFORMATION

These highlights do not include all the information needed to use MENQUADFI® safely and effectively. See full prescribing information for MENQUADFI.
MenQuadfi, Meningococcal (Groups A, C, Y, W) Conjugate Vaccine
Solution for Intramuscular Injection
Initial U.S. Approval: 2020

1 INDICATIONS AND USAGE

MenQuadfi is a vaccine indicated for active immunization for the prevention of invasive meningococcal disease caused by Neisseria meningitidis serogroups A, C, W, and Y. MenQuadfi is approved for use in individuals 2 years of age and older. (1)

MenQuadfi does not prevent N. meningitidis serogroup B disease.

2 DOSAGE AND ADMINISTRATION

0.5 mL dose for intramuscular injection. (2)

Primary Vaccination

- Individuals 2 years of age and older: a single dose.

Booster Vaccination

- A single dose of MenQuadfi may be administered to individuals 15 years of age and older who are at continued risk for meningococcal disease if at least 4 years have elapsed since a prior dose of meningococcal (groups A, C, W, Y) conjugate vaccine.

3 DOSAGE FORMS AND STRENGTHS

Solution for injection in 0.5 mL single-dose vial. (3)

4 CONTRAINDICATIONS

Severe allergic reaction to any component of the vaccine, or after a previous dose of MenQuadfi or any other tetanus toxoid-containing vaccine. (4)

6 ADVERSE REACTIONS

Most commonly reported adverse reactions (≥10%) following a primary dose were as follows:

- Children 2 through 9 years of age, pain (38.6%), erythema (22.6%), and swelling (13.8%) at the injection site; malaise (21.1%), myalgia (20.1%), and headache (12.5%). (6)
- Adolescents aged 10 through 17 years of age, injection site pain (34.8%–45.2%), myalgia (27.4%–35.3%), headache (26.5%–30.2%), and malaise (19.4%–26.0%). (6)
- Adults aged 18 through 55 years, injection site pain (41.9%), myalgia (35.6%), headache (29.0%), and malaise (22.9%). (6)
- Adults 56 years of age and older, pain at the injection site (25.5%), myalgia (21.9%), headache (19.0%), and malaise (14.5%). (6)

In adolescents and adults, rates of solicited adverse reactions following a booster dose were comparable to those observed following primary vaccination. (6)

To report SUSPECTED ADVERSE REACTIONS, contact Sanofi Pasteur Inc., Discovery Drive, Swiftwater, PA 18370 at 1-800-822-2463 (1-800-VACCINE) or VAERS at 1-800-822-7967 or www.vaers.hhs.gov.

FULL PRESCRIBING INFORMATION

1 INDICATIONS AND USAGE

MenQuadfi® is a vaccine indicated for active immunization for the prevention of invasive meningococcal disease caused by Neisseria meningitidis serogroups A, C, W, and Y. MenQuadfi is indicated for use in individuals 2 years of age and older.

MenQuadfi does not prevent N. meningitidis serogroup B disease.

2 DOSAGE AND ADMINISTRATION

2.1 Preparation for Administration

MenQuadfi is a clear, colorless solution.

Parenteral drug products should be inspected visually for particulate matter and/or discoloration prior to administration, whenever solution and container permit. If any of these conditions exist, the vaccine should not be administered. Discard the vial with any unused portion.

2.2 Dose and Schedule

Administer MenQuadfi as a single 0.5 mL injection intramuscularly.

Primary Vaccination

- Individuals 2 years of age and older receive a single dose.

Booster Vaccination

- A single dose of MenQuadfi may be administered to individuals 15 years of age and older who are at continued risk for meningococcal disease if at least 4 years have elapsed since a prior dose of meningococcal (groups A, C, W, Y) conjugate vaccine.

3 DOSAGE FORMS AND STRENGTHS

MenQuadfi is a sterile solution for intramuscular injection supplied in 0.5 mL single-dose vials.

4 CONTRAINDICATIONS

Severe allergic reaction to any component of the vaccine, or after a previous dose of MenQuadfi or any other tetanus toxoid-containing vaccine [see Description (11)].

5 WARNINGS AND PRECAUTIONS

5.1 Management of Acute Allergic Reactions

Appropriate observation and medical treatment should always be readily available in case of an anaphylactic event following the administration of the vaccine.

5.2 Altered Immunocompetence

Reduced Immune Response

Some individuals with altered immunocompetence, including some individuals receiving immunosuppressant therapy, may have reduced immune responses to MenQuadfi.

Complement Deficiency

Persons with certain complement deficiencies and persons receiving treatment that inhibits terminal complement activation (for example, eculizumab) are at increased risk for invasive disease caused by N. meningitidis, including invasive disease caused by serogroups A, C, W, and Y, even if they develop antibodies following vaccination with MenQuadfi [see Clinical Pharmacology (12.1)].

5.3 Syncope

Syncope (fainting) can occur following, or even before, vaccination with MenQuadfi.

Procedures should be in place to prevent falling and injury and to manage syncope.

5.4 Guillain-Barré Syndrome

Guillain-Barré syndrome (GBS) has been reported in temporal relationship following administration of another U.S.-licensed meningococcal quadrivalent polysaccharide conjugate vaccine. The decision by the healthcare professional to administer MenQuadfi to persons with a history of GBS should take into account the expected benefits and potential risks.

5.5 Tetanus Immunization

Immunization with MenQuadfi does not substitute for routine tetanus immunization.

5.6 Limitations of Vaccine Effectiveness

Vaccination with MenQuadfi may not protect all vaccine recipients.

6 ADVERSE REACTIONS

6.1 Clinical Trials Experience

Because clinical trials are conducted under widely varying conditions, adverse reaction rates observed in the clinical trial(s) of a vaccine cannot be directly compared to rates in the clinical trial(s) of another vaccine and may not reflect the rates observed in practice.

The safety of a single dose of MenQuadfi in individuals 2 years of age and older was evaluated in five randomized, active-controlled, multi-center clinical studies conducted in the US and Puerto Rico. In these studies, a total of 4,919 participants received either a primary dose (N = 4517) or a booster dose (N = 402) of MenQuadfi and were included in the safety analyses.

Safety Monitoring

Participants were monitored for immediate reactions for 30 minutes following vaccination while at the study site. Solicited injection site and systemic reactions were recorded by participants or by parents/guardians in a diary card at home daily for 7 days following vaccination. All unsolicited adverse events that occurred within 30 days following vaccination were recorded by participants or by parents/guardians and collected by the study site at the next visit. Unsolicited adverse events that were medically attended (i.e., visits to an emergency room, or an unexpected visit to a health care provider), and all serious adverse events (SAEs) were collected for at least 6 months after vaccination.

Primary Vaccination Studies

Children 2 through 9 years of age

The safety of MenQuadfi in children 2 years through 9 years of age was evaluated in Study 1 (NCT03077438). The safety analysis set included 498 participants who received MenQuadfi and 494 participants who received Menveo [Meningococcal (Groups A, C, Y, and W-135) Oligosaccharide Diphtheria CRM197 Conjugate Vaccine]. Of the participants 2 through 9 years of age who received MenQuadfi (N = 498), 50.2% were 2 through 5 years of age, 49.8% were 6 through 9 years of age, 49.0% were female, 80.5% were White, 13.3% were Black or African American, 0.4% were Asian, 5.2% were of other racial groups, and 22.9% were of Hispanic or Latino ethnicity. There were no substantive differences in demographic characteristics between the vaccine groups.

The rates and severity of the solicited adverse reactions that occurred within 7 days following MenQuadfi compared with Menveo (Study 1) are presented in Table 1.

SAEs occurred at a rate of 1.4% following MenQuadfi and at a rate of 0.6% following Menveo during the entire study period. Most SAEs occurred more than 30 days following vaccination and were commonly occurring events in the general population in this age group. No SAEs were determined to be vaccine related.

Table 1: Percentages of Solicited Injection-Site Reactions and Systemic Adverse Reactions within 7 Days after Vaccination with MenQuadfi or Menveo in Children 2 through 9 Years of Age (Study 1) [Clinical trial identifier NCT03077438]
 | MenQuadfi (N [N is the number of vaccinated participants with available data for the events listed] =484-487) % |  | Menveo (N=479-486) %
Adverse Reactions | Any | Grade 3 | Any | Grade 3
Local Reactions
Injection Site Pain [Grade 3: Unable to perform usual activities] | 38.6 | 0.6 | 42.4 | 1.0
Injection Site Erythema [Any: > 0 mm; Grade 3: ≥ 50 mm] | 22.6 | 3.1 | 31.5 | 9.9
Injection Site Swelling | 13.8 | 1.4 | 21.5 | 5.6
Systemic Reactions
Myalgia [Grade 3: Prevents daily activity] | 20.1 | 0.4 | 23.0 | 0.8
Malaise | 21.1 | 1.8 | 20.4 | 1.0
Headache | 12.5 | 0.0 | 11.5 | 0.4
Fever [Any: ≥ 100.4°F (38.0°C); Grade 3: ≥ 102.1°F (39.0°C)] | 1.9 | 0.0 | 2.7 | 0.4

Adolescents 10 through 17 years of age

The safety of MenQuadfi in adolescents 10 through 17 years of age was evaluated in two clinical trial studies Study 2 (NCT02199691) and Study 3 (NCT02842853). The safety analysis set in these two studies included 3,196 participants who received MenQuadfi alone (1,684 participants), MenQuadfi concomitantly with Adacel® [Tetanus Toxoid, Reduced Diphtheria Toxoid and Acellular Pertussis Vaccine, Adsorbed] (Tdap) and Gardasil® [Human Papillomavirus Quadrivalent (Types 6, 11, 16, and 18) Vaccine, Recombinant] (HPV) (392 participants), the concomitant vaccines without MenQuadfi (296 participants), or a U.S.-licensed comparator meningococcal vaccine (824 participants). The comparator meningococcal vaccine was either Menveo (501 participants) or Menactra® [Meningococcal (Groups A, C, Y, and W-135) Polysaccharide Diphtheria Toxoid Conjugate Vaccine] (323 participants).

Of the participants 10 through 17 years of age who received MenQuadfi (N = 1,684), 49.6% were female. Among those with reported race and ethnicity, 79.3% were White, 14.2% were Black or African American, 1.1% were Asian, 5.4% were of other racial groups, and 21.5% were of Hispanic or Latino ethnicity. Mean age was 11.9 years at time of administration. There were no substantive differences in demographic characteristics between the vaccine groups.

The rates and severity of the solicited adverse reactions that occurred within 7 days following MenQuadfi compared with Menveo and Menactra are presented in Table 2. The most common injection site and systemic reactions occurring after MenQuadfi administration (in Study 2 and Study 3) were injection site pain (45.2% and 34.8%) and myalgia (35.3% and 27.4%), respectively.

In Study 2, SAEs occurred at a rate of 0.8% following MenQuadfi and 0.8% following Menveo. In Study 3, SAEs occurred at a rate of 0.3% following MenQuadfi and 0.9% following Menactra. No SAEs were determined to be vaccine related.

Table 2: Percentages of Solicited Injection-Site Reactions and Systemic Adverse Reactions within 7 Days after Vaccination with MenQuadfi or Menveo in Individuals 10 through 17 Years of Age Study 2 [Clinical trial identifier NCT02199691] and MenQuadfi or Menactra in Individuals 10 through 17 Years of Age Study 3 [Clinical trial identifier NCT02842853]
 | Study 2 |  |  |  | Study 3
 | MenQuadfi (N [N is the number of vaccinated participants with available data for the events listed] =494-496) % |  | Menveo (N=488-491) % |  | MenQuadfi (N=1129-1159) % |  | Menactra (N=310-314) %
Adverse Reactions | Any | Grade 3 | Any | Grade 3 | Any | Grade 3 | Any | Grade 3
Local Reactions
Injection Site Pain [Grade 3: Prevents daily activity] | 45.2 | 1.4 | 42.5 | 1.0 | 34.8 | 1.8 | 41.4 | 2.2
Injection Site Erythema [Any: > 25 mm; Grade 3: > 100 mm] | 5.0 | 0.4 | 7.5 | 1.2 | 4.5 | 0.3 | 4.5 | 0.3
Injection Site Swelling | 5.4 | 0.2 | 6.5 | 0.4 | 4.1 | <0.1 | 4.8 | 0.0
Systemic Reactions
Myalgia | 35.3 | 1.6 | 35.2 | 1.8 | 27.4 | 1.9 | 31.2 | 1.9
Headache | 30.2 | 1.8 | 30.9 | 1.8 | 26.5 | 2.3 | 28.0 | 1.9
Malaise | 26.0 | 2.2 | 26.4 | 2.8 | 19.4 | 1.2 | 23.9 | 1.3
Fever [Any: ≥ 100.4°F (38.0°C); Grade 3: ≥ 102.1°F (39.0°C)] | 1.4 | 0.4 | 1.2 | 0.6 | 0.7 | 0.2 | 0.6 | 0.0

Among 296 participants who received Tdap and HPV concomitantly (without MenQuadfi) and 392 participants who received MenQuadfi concomitantly with Tdap and HPV, there were no notable differences in the rates of systemic solicited adverse reactions within 7 days following vaccination.

Dizziness within 30 minutes following vaccination was experienced by 1 (0.2%) participant who received MenQuadfi in Study 2 (NCT02199691) and 2 (0.2%) participants who received MenQuadfi in Study 3 (NCT02842853). Three participants in Study 2 experienced syncope within 30 minutes following vaccination: 1 (0.2%) participant who received Menveo, 1 (0.3%) participant who received MenQuadfi concomitantly with Tdap and HPV, and 1 (0.3%) participant who received Tdap and HPV concomitantly (without MenQuadfi). These events were non-serious and spontaneously resolved on the same day.

Adults 18 through 55 years of age

The safety of MenQuadfi in adults 18 through 55 years of age was evaluated in Study 3 (NCT02842853). The safety analysis set included 1,495 participants who received MenQuadfi and 312 participants who received Menactra. Of the participants 18 years through 55 years of age who received MenQuadfi (N = 1,495), 65.2% were female. Among those with reported race and ethnicity, 73.3% were White, 21.0% were Black or African American, 2.2% were Asian, 3.5% were of other racial groups, and 20.0% were of Hispanic or Latino ethnicity. Mean age was 39.4 years at time of administration.

The rates and severity of the solicited adverse reactions that occurred within 7 days following MenQuadfi compared with Menactra are presented in Table 3.

Dizziness within 30 minutes following vaccination was experienced by 5 (0.3%) participants who received MenQuadfi and 1 (0.3%) participant who received Menactra. These events were non-serious and spontaneously resolved on the same day.

SAEs occurred at a rate of 1.6% following MenQuadfi and at a rate of 0.6% following Menactra during the entire study period. No SAEs were determined to be vaccine related.

Table 3: Percentages of Solicited Injection-Site Reactions and Systemic Adverse Reactions within 7 Days after Vaccination with MenQuadfi or Menactra in Individuals 18 through 55 Years of Age (Study 3) [Clinical trial identifier NCT02842853]
 | MenQuadfi (N [N is the number of vaccinated participants with available data for the events listed] =1,441-1,460) % |  | Menactra (N=297-301) %
Adverse Reactions | Any | Grade 3 | Any | Grade 3
Local Reactions
Injection Site Pain [Grade 3: Prevents daily activity] | 41.9 | 1.9 | 35.0 | 1.3
Injection Site Erythema [Any: > 25 mm; Grade 3: > 100 mm] | 5.1 | 0.3 | 3.7 | 0.3
Injection Site Swelling | 4.3 | 0.2 | 3.4 | 0.3
Systemic Reactions
Myalgia | 35.6 | 3.6 | 31.2 | 2.3
Headache | 29.0 | 2.9 | 27.6 | 2.7
Malaise | 22.9 | 2.9 | 18.9 | 3.3
Fever [Any: ≥ 100.4°F (38.0°C); Grade 3: ≥ 102.1°F (39.0°C)] | 1.4 | 0.1 | 1.7 | 0.7

Adults 56 years of age and older

The safety of MenQuadfi in adults 56 years of age and older was evaluated in Study 4 (NCT02842866). The safety analysis set included 448 participants who received MenQuadfi intramuscularly and 453 participants who received a non-conjugate comparator meningococcal vaccine, Menomune® – A/C/Y/W-135 [Meningococcal Polysaccharide Vaccine, Groups A, C, Y, and W-135 Combined], subcutaneously. Of the participants 56 years of age and older who received MenQuadfi (N = 448), 44.4% were 56 through 64 years of age, 55.6% were 65 years of age and older, 57.6% were female, 86.6% were White, 11.6% were Black or African American, 1.1% were Asian, 0.4% were of other racial groups and 7.8% were of Hispanic or Latino ethnicity. Mean age was 67.0 years at time of administration.

The rates and severity of the solicited adverse reactions that occurred within 7 days following MenQuadfi compared with Menomune in Study 4 (NCT02842866) are presented in Table 4.

SAEs occurred at a rate of 3.3% following MenQuadfi and at a rate of 3.3% following Menomune during the entire study period. No SAEs were determined to be vaccine related.

Table 4: Percentages of Solicited Injection-Site Reactions and Systemic Adverse Reactions within 7 Days after Vaccination with MenQuadfi or Menomune in Individuals 56 Years of Age and Older Study 4 [Clinical trial identifier NCT02842866]
 | MenQuadfi (N [N is the number of vaccinated participants with available data for the events listed] =436-443) % |  | Menomune [Menomune was given subcutaneously] (N=449-451) %
Adverse Reactions | Any | Grade 3 | Any | Grade 3
Local Reactions
Injection Site Pain [Grade 3: Prevents daily activity] | 25.5 | 0.7 | 9.6 | 0.7
Injection Site Erythema [Any: > 25 mm; Grade 3: > 100 mm] | 5.2 | 0.2 | 0.0 | 0.0
Injection Site Swelling | 4.5 | 0.0 | 0.0 | 0.0
Systemic Reactions
Myalgia | 21.9 | 1.6 | 15.3 | 1.3
Headache | 19.0 | 0.7 | 14.6 | 0.7
Malaise | 14.5 | 1.4 | 11.3 | 1.8
Fever [Any: ≥ 100.4°F (38.0°C); Grade 3: ≥ 102.1°F (39.0°C)] | 2.1 | 0.2 | 0.4 | 0.0

Booster Vaccination Study

The safety of MenQuadfi in previously vaccinated adolescents and adults 15 years of age and older was evaluated in Study 5 (NCT02752906). All randomized participants had received a primary dose of either (Menveo or Menactra) 4 to 10 years previously. The safety analysis set included 402 participants who received a single booster dose of MenQuadfi (median age: 17.8 years) and 407 participants who received a single booster dose of Menactra (median age: 17.9 years). Of the participants who received MenQuadfi, 51.5% were female, 85.1% were White, 9.7% were Black, 2.7 % were Asian and 2.2 % were of other racial groups, and 15.7% were of Hispanic or Latino ethnicity.

The most commonly reported solicited adverse reactions (≥10%) within 7 days of MenQuadfi booster vaccination were injection site pain (44.7%) and headache (37.9%), myalgia (36.7%), and malaise (27.6%). The majority of solicited adverse reactions were Grade 1 or 2 and resolved within 3 days. Compared with recipients of a Menactra booster dose, recipients of a MenQuadfi booster dose had higher rates of injection site erythema (MenQuadfi 5.0%, Menactra 1.5%) and swelling (MenQuadfi 4.0%, Menactra 0.7%). Overall rates of solicited adverse reactions were comparable to those observed in unvaccinated adolescents and adults after a single MenQuadfi dose.

SAEs occurred at a rate of 1.2% following MenQuadfi and at a rate of 1.0% following Menactra during the entire study period. No SAEs were determined to be vaccine related.

7 DRUG INTERACTIONS

7.1 Concomitant Administration with Other Vaccines

In a clinical trial in adolescents 10 through 17 years of age, MenQuadfi was administered concomitantly with Tdap and HPV [see Adverse Reactions (6) and Clinical Studies (14.3)].

Lower geometric mean antibody concentrations (GMCs) for antibodies to the pertussis antigens filamentous hemagglutinin (FHA), pertactin (PRN) and fimbriae (FIM) were observed when MenQuadfi was co-administered with Tdap and HPV, compared to concomitant administration of Tdap and HPV (without MenQuadfi) [see Clinical Studies (14.3)].

7.2 Immunosuppressive Treatments

Immunosuppressive therapies may reduce the immune response to MenQuadfi [see Warnings and Precautions (5)].

8 USE IN SPECIFIC POPULATIONS

8.1 Pregnancy

Pregnancy Exposure Registry

There is a pregnancy exposure registry that monitors pregnancy outcomes in women exposed to MenQuadfi during pregnancy. To enroll in or obtain information about the registry, call Sanofi Pasteur at 1-800-822-2463.

Risk Summary

All pregnancies have a risk of birth defect, loss, or other adverse outcomes. In the US general population, the estimated background risk of major birth defects and miscarriage in clinically recognized pregnancies is 2-4% and 15-20%, respectively.

There are no clinical studies of MenQuadfi in pregnant women. Available human data on MenQuadfi administered to pregnant women are insufficient to inform vaccine-associated risks in pregnancy. A developmental toxicity study in female rabbits administered a full human dose (0.5 mL) prior to mating and during gestation period revealed no evidence of harm to the fetus due to MenQuadfi (see Animal Data).

Data

Animal Data

In a developmental toxicity study, female rabbits received a human dose of MenQuadfi by intramuscular injection on five occasions: 30 days and 10 days prior to mating, gestation days 6, 12 and 27. No adverse effects on pre-weaning development up to post-natal day 35 were observed. There were no vaccine-related fetal malformations or variations observed.

8.2 Lactation

Risk Summary

It is not known whether MenQuadfi is excreted in human milk. Data are not available to assess the effects of MenQuadfi on the breastfed infant or on milk production/excretion.

The developmental and health benefits of breastfeeding should be considered along with the mother's clinical need for MenQuadfi and any potential adverse effects on the breastfed child from MenQuadfi or from the underlying maternal condition. For preventive vaccines, the underlying maternal condition is susceptibility to disease prevented by the vaccine.

8.4 Pediatric Use

Safety and effectiveness of MenQuadfi have not been established in individuals younger than 2 years of age in the US.

8.5 Geriatric Use

A total of 249 participants 65 years of age and older, including 71 participants 75 years of age or older, in Study 4 received one dose of MenQuadfi [see Adverse Reactions (6.1) and Clinical Studies (14.1)].

MenQuadfi recipients ≥ 65 years of age had lower GMTs and seroresponse rates for all serogroups compared to MenQuadfi recipients 56 through 64 years of age [see Clinical Studies (14.1)].

11 DESCRIPTION

MenQuadfi is a sterile liquid vaccine administered by intramuscular injection that contains Neisseria meningitidis serogroup A, C, W, and Y capsular polysaccharide antigens that are individually conjugated to tetanus toxoid protein. N. meningitidis A, C, W, and Y strains are cultured on Mueller Hinton agar medium and grown in Watson Scherp medium. The polysaccharides are extracted from the N. meningitidis cells and purified by centrifugation, detergent precipitation, alcohol precipitation, solvent extraction, and diafiltration. To prepare the polysaccharides for conjugation, Serogroup A is activated with carbonyldiimidazole (CDI), derivatized with adipic acid dihydrazide (ADH), and purified by diafiltration. Serogroups C, W, and Y are depolymerized, activated with periodate, and purified by diafiltration.

Clostridium tetani is fermented in media to generate tetanus toxin, which is purified by ammonium sulfate precipitation to yield purified tetanus toxin (PTT) and detoxified with formaldehyde to yield purified tetanus protein (PTP). The PTP is then concentrated and filtered to yield concentrated tetanus protein (CTP). The activated/derivatized polysaccharides are covalently linked to tetanus toxoid and purified by chromatography and serial diafiltration. The four meningococcal components, present as individual serogroup-specific glycoconjugates, compose the final formulated vaccine.

MenQuadfi is manufactured as a sterile, clear, colorless solution. Each 0.5 mL dose of vaccine contains 10 microgram each of meningococcal A, C, W, and Y polysaccharide antigens conjugated to approximately 55 micrograms tetanus toxoid protein carrier; 3.35 mg sodium chloride (0.67%), and 1.23 mg sodium acetate (30 mM). Potency of MenQuadfi is determined by quantifying the amount of each polysaccharide antigen that is conjugated to tetanus toxoid protein and the amount of unconjugated polysaccharide present.

No preservative or adjuvant is added during manufacture. Each 0.5 mL dose may contain residual amounts of formaldehyde of less than 3 mcg/mL, by calculation.

The vial in which the vaccine components are contained is composed of USP Type I borosilicate glass. The vial stopper is a chlorobutyl synthetic polyisoprene blend stopper (not made with natural rubber latex).

12 CLINICAL PHARMACOLOGY

12.1 Mechanism of Action

Invasive meningococcal disease (IMD) is caused by the bacterium N. meningitidis, a gram-negative diplococcus found exclusively in humans. The presence of bactericidal anti-capsular meningococcal antibodies in serum has been associated with protection from IMD. MenQuadfi induces the production of bactericidal antibodies specific to the capsular polysaccharides of N. meningitidis serogroups A, C, W, and Y.

13 NONCLINICAL TOXICOLOGY

13.1 Carcinogenesis, Mutagenesis, Impairment of Fertility

MenQuadfi has not been evaluated for carcinogenic or mutagenic potential or for impairment of male fertility. MenQuadfi administered to female rabbits had no effects on fertility [see Use in Specific Population (8.1)].

14 CLINICAL STUDIES

To infer effectiveness of MenQuadfi, the immunogenicity in persons 2 years of age and older was evaluated using a serogroup-specific serum bactericidal assay with exogenous human complement (hSBA). The hSBA responses following a single dose of MenQuadfi for primary vaccination were assessed in four studies, and the hSBA responses following a single dose of MenQuadfi for booster vaccination were assessed in one study. Serum was collected at baseline and 30 days post-vaccination to measure antibodies with hSBA. The hSBA geometric mean titers (GMTs) and proportion of participants who achieved hSBA seroresponse (defined below) were evaluated.

- Seroresponse rate for each serogroup: the proportion of participants with an hSBA
  - pre-vaccination titer < 1:8 who achieved a post-vaccination titer ≥ 1:16, or
  - pre-vaccination titer ≥ 1:8 who achieved a post-vaccination titer at least 4-fold greater than the pre-vaccination titer.

Non-inferiority of MenQuadfi seroresponse rates versus those for comparator vaccines was demonstrated for all 4 serogroups in individuals 2 years of age and older who received a primary vaccination and in individuals 15 years of age and older who received a booster vaccination at least 4 years following a previous dose of a meningococcal (groups A, C, W, Y) conjugate vaccine.

14.1 Primary Vaccination

Immunogenicity in Children 2 through 9 Years of Age

Immunogenicity of MenQuadfi compared to Menveo in participants 2 through 9 years of age was evaluated in Study 1 (NCT03077438). The hSBA seroresponse rate and GMTs are presented in Table 5.

Immune non-inferiority, based on seroresponse rates, was demonstrated for MenQuadfi as compared to Menveo for all four serogroups.

Table 5: Comparison of Bactericidal Antibody Responses to MenQuadfi and Menveo 30 Days after Vaccination of Participants 2 through 9 Years of Age (Study 1) [Clinical trial identifier NCT03077438]
Endpoint [Seroresponse rate (primary endpoint) for each serogroup: the proportion of participants with an hSBA pre-vaccination titer < 1:8 who achieved a post-vaccination titer ≥ 1:16, or pre-vaccination titer ≥ 1:8 who achieved a post-vaccination titer at least 4-fold greater than the pre-vaccination titer.] | MenQuadfi (95% CI) | Menveo (95% CI) | Percent difference MenQuadfi minus Menveo [Overall non-inferiority would be demonstrated if the lower limit of the 2-sided 95% CI is > -10% for all four serogroups.] (95% CI)
A | N=455-456 | N=458
% Participants achieving Seroresponse | 55.4 (50.7; 60.0) | 47.8 (43.2; 52.5) | 7.6 (1.1, 14.0)
GMT | 25 (22; 28) | 23 (20; 26)
C | N=458 | N=458-459
% Participants achieving Seroresponse | 95.2 (92.8; 97.0) | 47.8 (43.2; 52.5) | 47.4 (42.2, 52.2)
GMT | 238 (209; 270) | 17.0 (14; 20)
W | N=458 | N=459
% Participants achieving Seroresponse | 78.8 (74.8; 82.5) | 64.1 (59.5; 68.4) | 14.8 (8.9, 20.5)
GMT | 38 (34; 42) | 26 (23; 30)
Y | N=458 | N=459
% Participants achieving Seroresponse | 91.5 (88.5; 93.9) | 79.3 (75.3; 82.9) | 12.2 (7.7, 16.7)
GMT | 69 (61; 77) | 44 (38; 50)
N: number of participants in per-protocol analysis set with valid serology results.
95% CI of the single proportion calculated from the exact binomial method.
95% CI of the difference calculated from the Wilson Score method without continuity correction.

Immunogenicity in Adolescents 10 through 17 Years of Age

Immunogenicity of MenQuadfi compared to Menveo in participants 10 through 17 years of age was evaluated in Study 2 (NCT02199691). Study 2 was conducted in healthy meningococcal vaccine naïve participants and evaluated seroresponse rates following administration with either MenQuadfi alone, Menveo alone, MenQuadfi co-administered with Tdap, and HPV, or Tdap and HPV alone. The hSBA seroresponse rate and GMTs for Study 2 are presented in Table 6.

Immune non-inferiority, based on seroresponse, was demonstrated for MenQuadfi as compared to Menveo for all four serogroups.

Study 2 (NCT02199691) was conducted in healthy meningococcal vaccine naïve male and female participants and evaluated seroresponses following administration with either MenQuadfi alone; Menveo alone; MenQuadfi co-administered with Tdap, and HPV; or Tdap and HPV alone. The hSBA seroresponse rate and GMTs for the MenQuadfi alone and Menveo alone groups are presented in Table 6.

Table 6: Comparison of Bactericidal Antibody Responses to MenQuadfi and Menveo 30 Days after Vaccination of Participants 10 through 17 Years of Age Study 2 [Clinical trial identifier NCT02199691]
Endpoint [Seroresponse rate (primary endpoint) for each serogroup: the proportion of participants with an hSBA pre-vaccination titer < 1:8 who achieved a post-vaccination titer ≥ 1:16, or pre-vaccination titer ≥ 1:8 who achieved a post-vaccination titer at least 4-fold greater than the pre-vaccination titer.] | MenQuadfi (95% CI) | Menveo (95% CI) | Percent difference MenQuadfi minus Menveo [Overall non-inferiority would be demonstrated if the lower limit of the 2-sided 95% CI is > -10% for all four serogroups.] (95% CI)
A | N=463 | N=464
% Participants achieving Seroresponse | 70.2 (65.8; 74.3) | 60.3 (55.7; 64.8) | 9.8 (3.7;15.9)
GMT | 44 (39; 50) | 35 (30; 41)
C | N=462 | N=463
% Participants achieving Seroresponse | 96.1 (93.9, 97.7) | 61.6 (57.0, 66.0) | 34.5 (29.7; 39.3)
GMT | 387 (329; 456) | 51 (41; 64)
W | N=463 | N=464
% Participants achieving Seroresponse | 84.2 (80.6; 87.4) | 56.0 (51.4; 60.6) | 28.2 (22.5; 33.7)
GMT | 87 (78; 97) | 36 (32; 41)
Y | N=462-463 | N=464
% Participants achieving Seroresponse | 91.1 (88.2; 93.6) | 66.8 (62.3;71.1) | 24.3 (19.2; 29.3)
GMT | 76 (66; 87) | 28 (24; 32)
N: number of participants in per-protocol analysis set with valid serology results.
95% CI of the single proportion calculated from the exact binomial method.
95% CI of the difference calculated from the Wilson Score method without continuity correction.

Study 3 evaluated the immunogenicity of MenQuadfi (N=1097-1098) compared to Menactra (N=300) in healthy meningococcal-naïve participants 10 through 17 years of age. Seroresponse rates for MenQuadfi were noninferior to those of Menactra for all serogroups based on the same noninferiority criteria defined for Study 2.

Immunogenicity in Adults 18 through 55 Years of Age

Immunogenicity of MenQuadfi compared to Menactra in participants 18 through 55 years of age was evaluated in Study 3 (NCT02842853). The hSBA seroresponse rate and GMTs are presented in Table 7.

Immune non-inferiority, based on seroresponse rates, was demonstrated for MenQuadfi as compared to Menactra for all four serogroups.

Table 7: Comparison of Bactericidal Antibody Responses to MenQuadfi and Menactra 30 Days after Vaccination of Participants 18 through 55 Years of Age Study 3 [Clinical trial identifier NCT02842853]
Endpoint [Seroresponse rate (primary endpoint) for each serogroup: the proportion of participants with an hSBA pre-vaccination titer < 1:8 who achieved a post-vaccination titer ≥ 1:16, or pre-vaccination titer ≥ 1:8 who achieved a post-vaccination titer at least 4-fold greater than the pre-vaccination titer.] | MenQuadfi (95% CI) | Menactra (95% CI) | Percent difference MenQuadfi minus Menactra [The overall non-inferiority would be demonstrated if the lower limit of the 2-sided 95% CI is > -10% for all four serogroups.] (95% CI)
A | N=1,406-1,408 | N=293
% Participants achieving Seroresponse | 73.5 (71.2; 75.8) | 53.9 (48.0; 59.7) | 19.6 (13.5; 25.8)
GMT | 106 (97; 117) | 52 (43; 64)
C | N=1,406-1,408 | N=293
% Participants achieving Seroresponse | 83.4 (81.4; 85.3) | 42.3 (36.6; 48.2) | 41.1 (35.0; 46.9)
GMT | 234 (210; 261) | 37 (29; 49)
W | N=1,408-1,410 | N=293
% Participants achieving Seroresponse | 77.0 (74.7; 79.2) | 50.2 (44.3; 56.0) | 26.8 (20.7; 32.9)
GMT | 76 (69; 83) | 33 (26; 42)
Y | N=1,408-1,410 | N=293
% Participants achieving Seroresponse | 88.1 (86.3; 89.8) | 60.8 (54.9; 66.4) | 27.4 (21.7; 33.3)
GMT | 219 (200; 239) | 55 (42; 70)
N: number of participants in per-protocol analysis set with valid serology results.
95% CI of the single proportion calculated from the exact binomial method.
95% CI of the difference calculated from the Wilson Score method without continuity correction.

Immunogenicity in Adults 56 Years of Age and Older

Immunogenicity of MenQuadfi compared to Menomune in participants 56 years and older was evaluated in Study 4 (NCT02842866).

Enrollment was stratified by age category: 56 through 64 years of age (44.3%), 65 through 74 years of age (39.7%), and 75 years of age and older (15.9%). The overall mean age of participants who received MenQuadfi was 66.9 years; range: 56 through 89.8 years of age. The mean age for participants in the 56 through 64 years age stratum who received MenQuadfi was 60.4 years, the mean age for participants ≥ 65 years age stratum who received MenQuadfi was 72.2 years.

The hSBA seroresponse rate and GMTs are presented in Table 8.

Immune non-inferiority, based on seroresponse rates, was demonstrated for MenQuadfi as compared to Menomune for all four serogroups.

Table 8: Comparison of Bactericidal Antibody Responses to MenQuadfi and Menomune in Naïve Older Adults and Elderly 30 Days after Vaccination Study 4 [Clinical trial identifier NCT02842866]
Endpoint [Seroresponse rate (primary endpoint) for each serogroup: the proportion of participants with an hSBA pre-vaccination titer < 1:8 who achieved a post-vaccination titer ≥ 1:16, or pre-vaccination titer ≥ 1:8 who achieved a post-vaccination titer at least 4-fold greater than the pre-vaccination titer.] | MenQuadfi (95% CI) | Menomune (95% CI) | Percent difference MenQuadfi minus Menomune [The overall non-inferiority would be demonstrated if the lower limit of the 2-sided 95% CI is > -10% for all four serogroups.] (95% CI)
A | N=433 | N=431
% Participants achieving Seroresponse | 58.2 (53.4; 62.9) | 42.5 (37.7; 47.3) | 15.7 (9.08; 22.2)
GMT | 55 (47; 65) | 31 (27; 37)
C | N=433 | N=431
% Participants achieving Seroresponse | 77.1 (72.9; 81.0) | 49.7 (44.8; 54.5) | 27.5 (21.2; 33.5)
GMT | 101 (84; 123) | 25 (21; 30)
W | N=433 | N=431
% Participants achieving Seroresponse | 62.6 (57.8; 67.2) | 44.8 (40.0; 49.6) | 17.8 (11.2; 24.2)
GMT | 28 (24; 33) | 15 (13; 18)
Y | N=433 | N=431
% Participants achieving Seroresponse | 74.4 (70.0; 78.4) | 43.4 (38.7; 48.2) | 31.0 (24.6; 37.0)
GMT | 69 (59; 81) | 21 (17; 25)
N: number of participants in per-protocol analysis set with valid serology results.
95% CI of the single proportion calculated from the exact binomial method.
95% CI of the difference calculated from the Wilson Score method without continuity correction.

14.2 Booster

Immunogenicity of a booster dose of MenQuadfi compared to a booster dose of Menactra was evaluated in Study 5 (NCT02752906). The study-enrolled participants 15 years of age and older who had received a primary dose of Menveo or Menactra 4 to 10 years previously.

Immune non-inferiority, based on seroresponse rates, was demonstrated for MenQuadfi as compared to Menactra for all four serogroups.

For a description of study design and number of participants, see section 6.1 Booster Vaccination Study. The primary immunogenicity endpoint was hSBA seroresponse to each serogroup 30 days following booster vaccination with MenQuadfi or Menactra given to participants who received a prior dose of Menveo or Menactra 4 to 10 years ago. Seroresponse was defined as the proportion of participants with an hSBA pre-vaccination titer < 1:8 who achieved a post-vaccination titer ≥ 1:16, or pre-vaccination titer ≥ 1:8 who achieved a post-vaccination titer at least 4-fold greater than the pre-vaccination titer. The other endpoints included the proportions of participants with post-vaccination hSBA ≥1:8 and the hSBA GMTs for each serogroup. These endpoints were also evaluated at 6 days post vaccination in a subset.

Seroresponse rates at Day 30 following booster vaccination with MenQuadfi were 92.2% for serogroup A, 97.1% for serogroup C, 98.2% for serogroup W, and 97.4% for serogroup Y, as compared to 87.1% for serogroup A, 91.8% for serogroup C, 90.7% for serogroup W, and 95.6% for serogroup Y, following booster vaccination with Menactra. At Day 6, following booster vaccination with MenQuadfi, seroresponse rates were 72.7%, 83.6%, 94.5%, and 90.9% for serogroups A, C, W, and Y, respectively.

The hSBA GMTs were 173, 334, 499, and 302 for serogroups A, C, W, and Y at Day 6, and 497, 2618, 1747, and 2070, respectively, for the 4 serogroups at Day 30 following booster dose of MenQuadfi.

Overall, similar seroresponse rates were observed for those participants who received booster vaccination with Menactra.

14.3 Immunogenicity of Concomitantly Administered Vaccines

Concomitant administration of MenQuadfi with Tdap and HPV in adolescents 10 through 17 years was evaluated in Study 2 (NCT02199691). In this randomized study, 503 participants received MenQuadfi alone, 392 received MenQuadfi coadministered with Tdap and HPV, 296 received Tdap and HPV alone. A fourth group received Menveo alone (N=501).

No evidence of interference in hSBA seroresponse rates was observed when MenQuadfi was coadministered with Tdap and HPV. Antibody responses to HPV, and to the tetanus and diphtheria antigens were similar when Tdap and HPV were administered with and without MenQuadfi. Anti-pertussis GMC responses were non-inferior for the pertussis toxoid antigen, but did not meet non-inferiority for the FHA, PRN, and FIM antigens. The clinical relevance of the diminished responses to the pertussis antigens is unknown.

16 HOW SUPPLIED/STORAGE AND HANDLING

Product: 50090-6180

NDC: 50090-6180-1 .5 mL in a VIAL, SINGLE-DOSE / 5 in a CARTON

17 PATIENT COUNSELING INFORMATION

Vaccine Information Statements are required by the National Childhood Vaccine Injury Act of 1986 to be given prior to immunization to the patient, parent, or guardian. These materials are available free of charge at the Centers for Disease Control and Prevention (CDC) website (www.cdc.gov/vaccines). Inform the patients, parents or guardians about:

- Potential benefits and risks of immunization with MenQuadfi.
- Potential for adverse reactions that have been temporally associated with administration of MenQuadfi or other vaccines containing similar components.
- Reporting any adverse reactions to their healthcare provider.
- The Sanofi Pasteur Inc. Pregnancy Registry, as appropriate [see Pregnancy (8.1)].

MenQuadfi is a registered trademark of Sanofi Pasteur Inc.
Menactra, Adacel and Menomune are registered trademarks of Sanofi, its affiliates and/or its subsidiaries.
Menveo is a registered trademark of GlaxoSmithKline Biologicals S.A.
Gardasil is a registered trademark of Merck Sharp & Dohme Corp.

Manufactured by:
Sanofi Pasteur Inc.
Swiftwater PA 18370 USA

© 2021, Sanofi Pasteur Inc. - All rights reserved
R5-0622